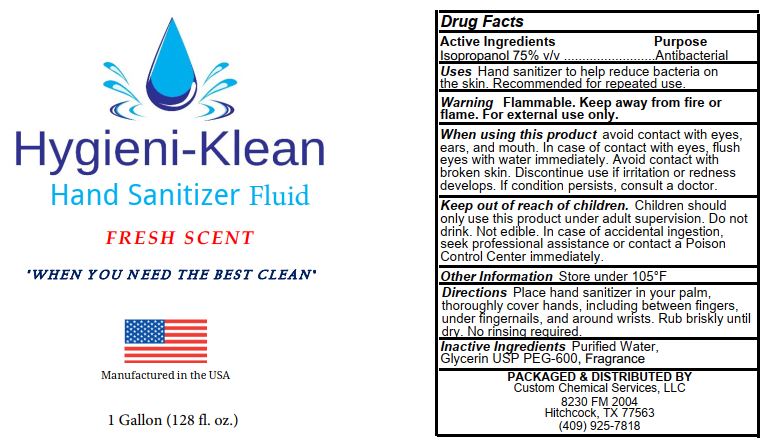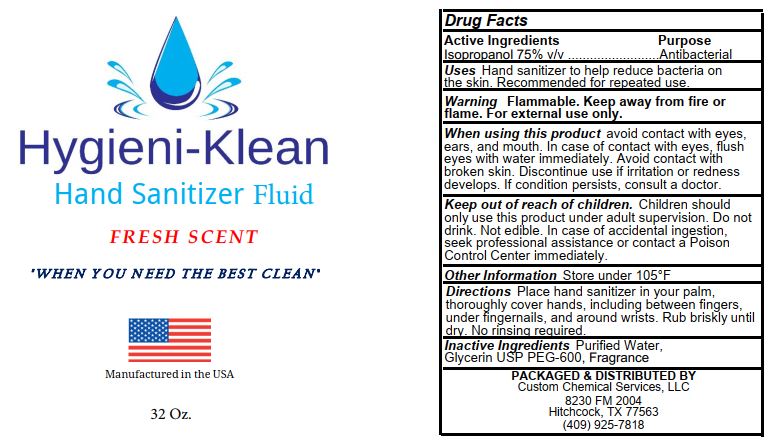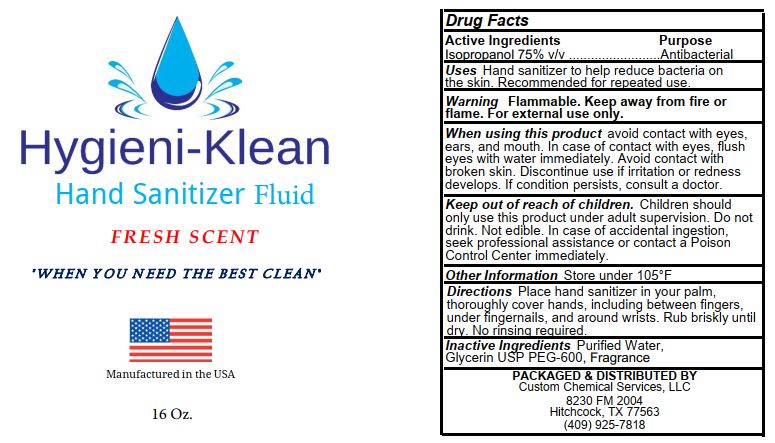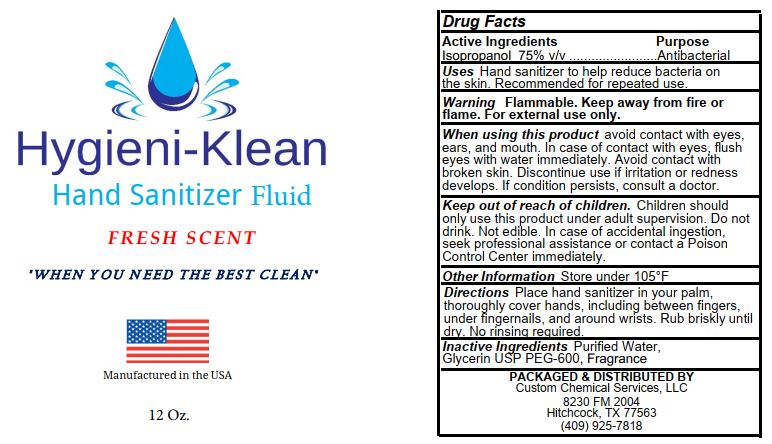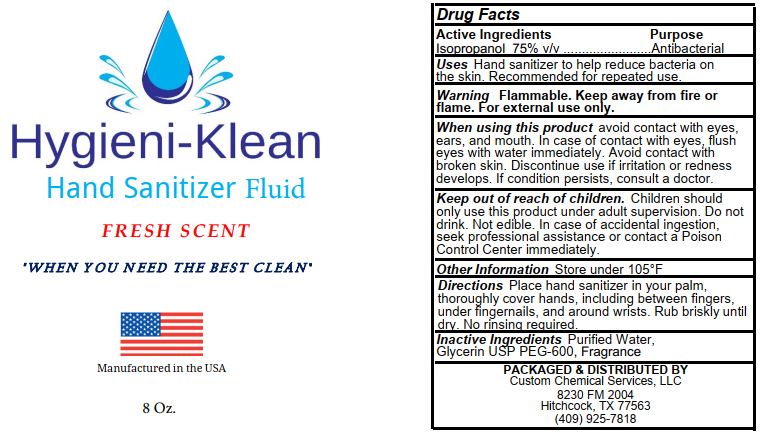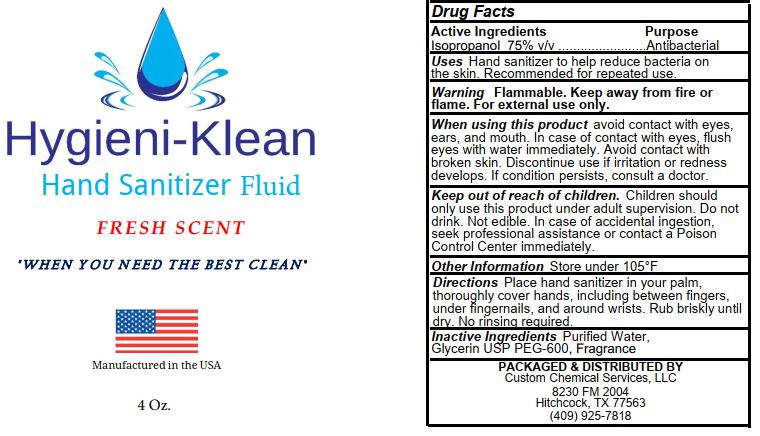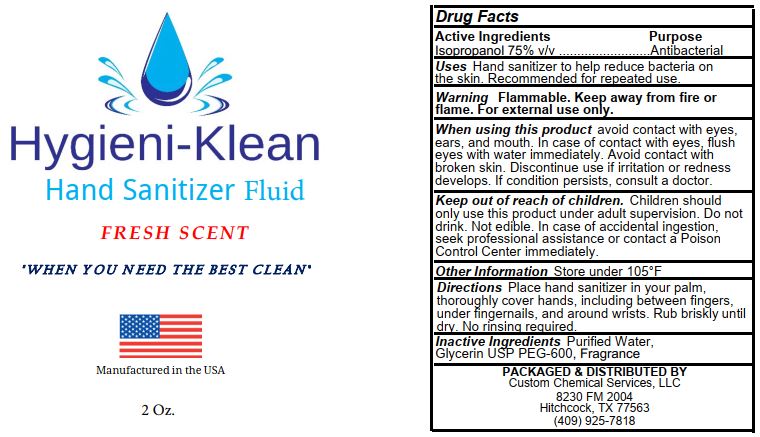 DRUG LABEL: Hygieni-Klean Hand Sanitizer Fluid Fresh
NDC: 78174-023 | Form: LIQUID
Manufacturer: Custom Chemical Services, LLC
Category: otc | Type: HUMAN OTC DRUG LABEL
Date: 20210427

ACTIVE INGREDIENTS: ISOPROPYL ALCOHOL 75.0271 L/100 L
INACTIVE INGREDIENTS: GLYCERIN 0.067 L/100 L; POLYETHYLENE GLYCOL 600 0.0409 L/100 L; water 24.7832 L/100 L; FRAGRANCE CUCUMBER ALOE ORC1802955 0.0818 1/100 L

Active Ingredients

Isopropanol 75% v/v

Purpose

Antibacterial

INDICATIONS AND USAGE

Uses Hand sanitizer to help reduce bacteria on the skin. Recommended for repeated use.

WARNINGS

Warning Flammable. Keep away from fire or flame. For external use only.

When using this product avoid contact with eyes, ears, and mouth. In case of contact with eyes, flush eyes with water immediately. Avoid contact with broken skin. Discontinue use if irritation or redness develops. If condition persists, consult a doctor.

Keep out of reach of children. Children should only use this product under adult supervison. Do not drink. Not edible. In case of accidential ingestion, seek professional assistance or contact a Poison Control Center immediately.

Other Information Store under 105°F.

DOSAGE AND ADMINISTRATION

Directions Place hand sanitizer in your palm, thoroughly cover hands, including between fingers, under fingernails, and around wrists. Rub briskly until dry. No rinsing required.

INACTIVE INGREDIENT

Inactive Ingredients Purified water, Glycerin USP, PEG-600, Fragrance

PACKAGE LABEL

01 – 1 Gallon:

02 – 32 oz:

03 – 16 oz:

04 – 12 oz:

05 – 8 oz:

06 – 4 oz:

07 – 2 oz: